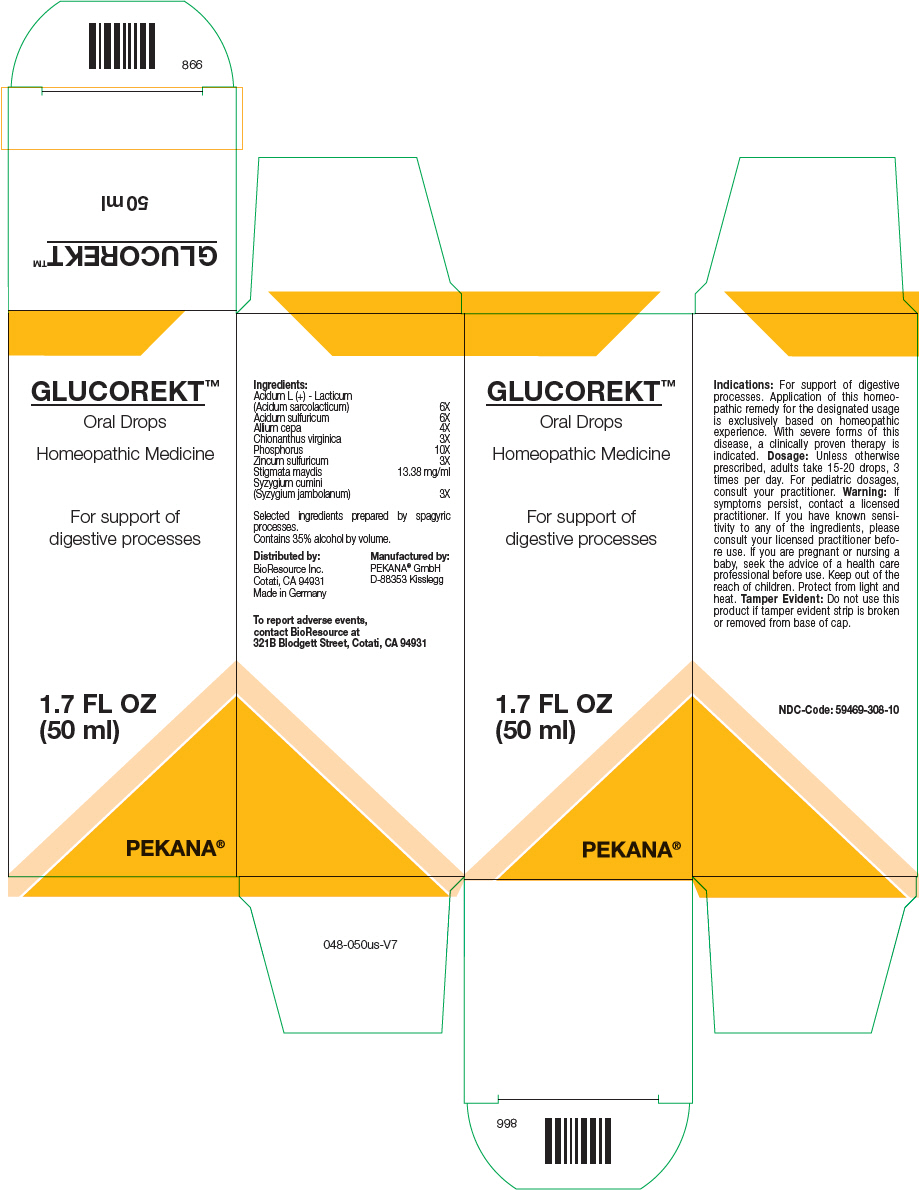 DRUG LABEL: GLUCOREKT
NDC: 59469-308 | Form: SOLUTION/ DROPS
Manufacturer: PEKANA Naturheilmittel GmbH
Category: homeopathic | Type: HUMAN OTC DRUG LABEL
Date: 20230111

ACTIVE INGREDIENTS: LACTIC ACID, DL- 6 [hp_X]/50 mL; SULFURIC ACID 6 [hp_X]/50 mL; ONION 4 [hp_X]/50 mL; CHIONANTHUS VIRGINICUS ROOT BARK 3 [hp_X]/50 mL; PHOSPHORUS 10 [hp_X]/50 mL; ZINC SULFATE HEPTAHYDRATE 3 [hp_X]/50 mL; CORN SILK 669 mg/50 mL; SYZYGIUM CUMINI FRUIT 3 [hp_X]/50 mL
INACTIVE INGREDIENTS: WATER; ALCOHOL

GLUCOREKT™

ACTIVE INGREDIENT

Ingredients:
Acidum L (+) - Lacticum (Acidum sarcolacticum) | 6X
Acidum sulfuricum | 6X
Allium cepa | 4X
Chionanthus virginica | 3X
Phosphorus | 10X
Zincum sulfuricum | 3X
Stigmata maydis | 13.38 mg/ml
Syzygium cumini (Syzygium jambolanum) | 3X

Selected ingredients prepared by spagyric processes.

INACTIVE INGREDIENT

Contains 35% alcohol by volume.

Indications

PURPOSE

For support of digestive processes. Application of this homeopathic remedy for the designated usage is exclusively based on homeopathic experience. With severe forms of this disease, a clinically proven therapy is indicated.

Dosage

Unless otherwise prescribed, adults take 15-20 drops, 3 times per day. For pediatric dosages, consult your practitioner.

Warning

ASK DOCTOR

If symptoms persist, contact a licensed practitioner. If you have known sensitivity to any of the ingredients, please consult your licensed practitioner before use. If you are pregnant or nursing a baby, seek the advice of a health care professional before use.

Keep out of the reach of children.

STORAGE AND HANDLING

Protect from light and heat.

Tamper Evident

Do not use this product if tamper evident strip is broken or removed from base of cap.

QUESTIONS

To report adverse events, contact BioResource at 321B Blodgett Street, Cotati, CA 94931

Distributed by:
BioResource Inc.
Cotati, CA 94931

Manufactured by:
PEKANA®GmbH
D-88353 Kisslegg

PRINCIPAL DISPLAY PANEL - 50 ml Bottle Box

GLUCOREKT™

Oral Drops

Homeopathic Medicine

For support of
digestive processes

1.7 FL OZ
(50 ml)

PEKANA®